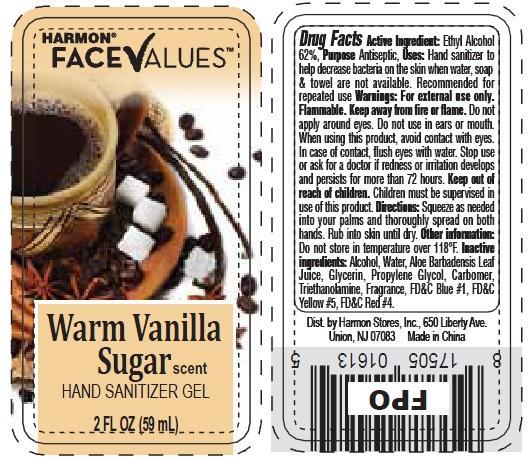 DRUG LABEL: Harmon Face Values Warm Vanilla Sugar Scent Hand Sanitizer
NDC: 63940-613 | Form: LIQUID
Manufacturer: Harmon Stores Inc.
Category: otc | Type: HUMAN OTC DRUG LABEL
Date: 20221117

ACTIVE INGREDIENTS: ALCOHOL 62 mL/100 mL
INACTIVE INGREDIENTS: WATER; ALOE VERA LEAF; GLYCERIN; TROLAMINE; FD&C BLUE NO. 1; FD&C YELLOW NO. 5; FD&C RED NO. 4

Harmon Face Values Warm Vanilla Sugar Scent Hand Sanitizer Gel

Active Ingredient

Ethyl Alcohol 62%

Purpose

Antibacterial

Uses

Hand sanitizer to help decrease bacteria on the skin when water, soap & towel are not available. Recommended for repeated use.

Warnings

For external use only. Flammable. Keep away from fire or flame. Do not apply around eyes. Do not use in ears or mouth. When using this product, avoid contact with eyes. In case of contact, flush eyes with water. Stop use or ask for a doctor if redness or irritation develops and persists for more than 72 hours.

Keep out of reach of children.

Children must be supervised in use of this product.

Directions

Squeeze as needed into your palms and thoroughly spread on both hands. Rub into skin until dry

Other Information

Do not store in temperatures over 118 degress F.

Inactive Ingredients

Alcohol, Water, Aloe barbadensis leaf juice, glycerin, propylene glycol, carbomer, triethanolamine, fragrance, FDandC Blue 1, FDandC yellow 5, FDandC red 4.

Dist. by Harmon Stores, Inc.,

650 Liberty Ave.

Union, NJ 07083 Made in China